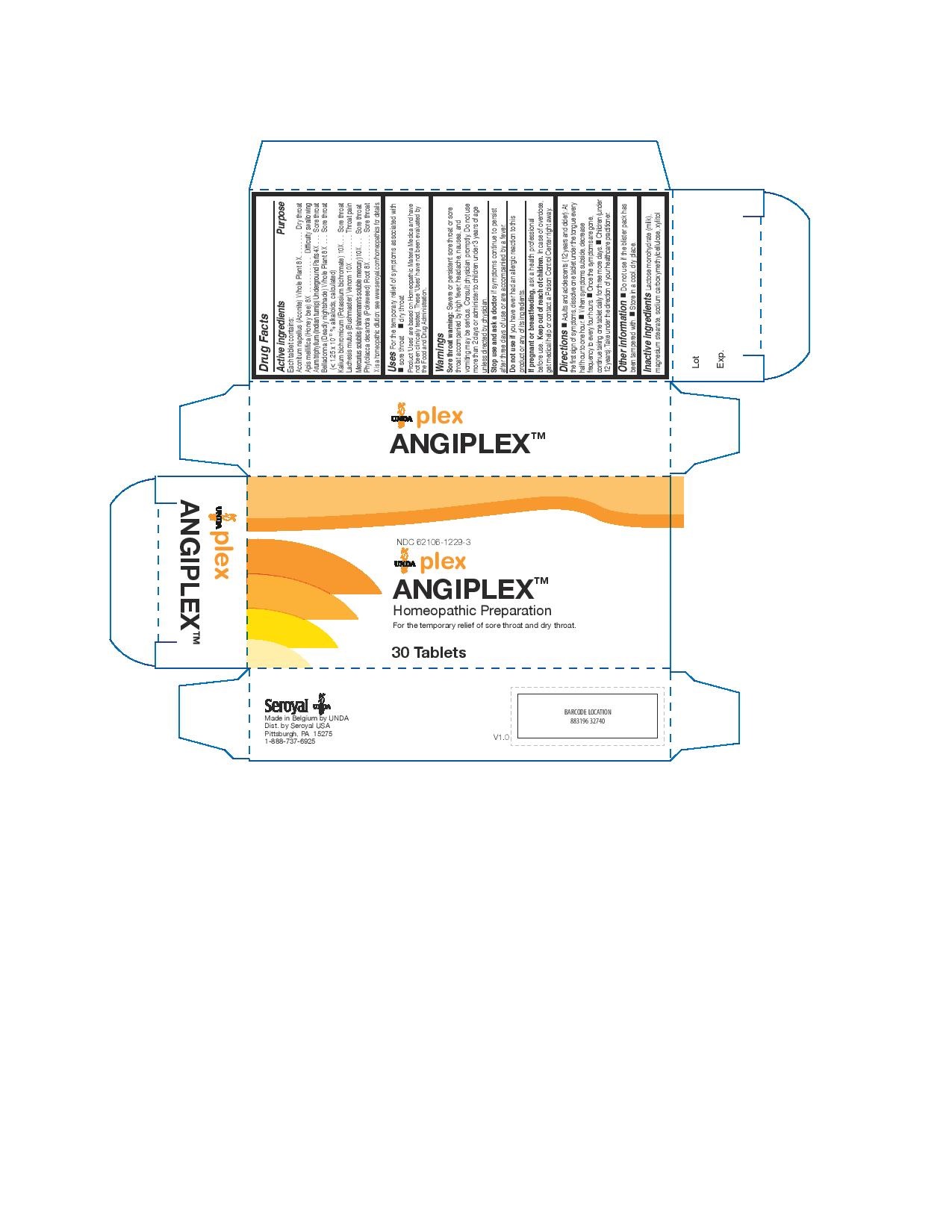 DRUG LABEL: Angiplex
NDC: 62106-1229 | Form: TABLET
Manufacturer: Seroyal USA
Category: homeopathic | Type: HUMAN OTC DRUG LABEL
Date: 20221109

ACTIVE INGREDIENTS: ARISAEMA TRIPHYLLUM ROOT 4 [hp_X]/1 1; ACONITUM NAPELLUS 8 [hp_X]/1 1; APIS MELLIFERA 8 [hp_X]/1 1; ATROPA BELLADONNA 8 [hp_X]/1 1; PHYTOLACCA AMERICANA ROOT 8 [hp_X]/1 1; POTASSIUM DICHROMATE 10 [hp_X]/1 1; LACHESIS MUTA VENOM 10 [hp_X]/1 1; MERCURIUS SOLUBILIS 10 [hp_X]/1 1
INACTIVE INGREDIENTS: XYLITOL; CARBOXYMETHYLCELLULOSE SODIUM; LACTOSE MONOHYDRATE; MAGNESIUM STEARATE

Angiplex

Active ingredients

Each tablet contains:
Aconitum napellus (Aconite) Whole Plant 8X
Apis mellifica (Honey bee) 8X
Arum triphyllum (Indian turnip) Underground Parts 4X
Belladonna (Deadly nightshade) Whole Plant 8X
(< 1.25 x 10-10 % alkaloids, calculated)
Kalium bichromicum (Potassium bichromate) 10X
Lachesis mutus (Bushmaster) Venom 10X
Mercurius solubilis (Hahnemann's soluble mercury) 10X
Phytolacca decandra (Pokeweed) Root 8X

Uses

For the temporary relief of symptoms associated with
sore throat

dry throat

Warnings

Sore throat warning: Severe or persistent sore throat or sore
throat accompanied by high fever, headache, nausea, and
vomiting may be serious. Consult physician promptly. Do not use
more than 2 days or administer to children under 3 years of age
unless directed by physician.
Stop use and ask a doctor if symptoms continue to persist
after three days of use or are accompanied by a fever.
Do not use if you have ever had an allergic reaction to this
product or any of its ingredients.
If pregnant or breastfeeding, ask a health professional
before use. Keep out of reach of children. In case of overdose,
get medical help or contact a Poison Control Center right away

Do not use if you have ever had an allergic reaction to this product or any of its ingredients.

PREGNANCY OR BREAST FEEDING

If pregnant or breastfeeding, ask a health professional before use.

Keep out of reach of children.

OVERDOSAGE

In case of overdose, get medical
help or contact a Poison Control Center right away.

Inactive ingredients

Lactose monohydrate (milk), magnesium stearate, sodium carboxymethylcellulose, xylitol

Other information

Do not use if the blister pack has been tampered with.

Store in a cool, dry place.

Directions

Adults and adolescents (12 years and older): At the first sign of symptoms, dissolve one tablet under the tongue every
half hour to one hour. When symptoms subside, decrease frequency to every four hours. Once the symptoms are gone,
continue taking one tablet daily for three more days.

Children (under 12 years): Take under the direction of your healthcare practitioner.

Uses

For the temporary relief of symptoms associated with
sore throat

dry throat

Directions

Adults and adolescents (12 years and older): At the first sign of symptoms, dissolve one tablet under the tongue every
half hour to one hour. When symptoms subside, decrease frequency to every four hours. Once the symptoms are gone,
continue taking one tablet daily for three more days.

Children (under 12 years): Take under the direction of your healthcare practitioner.

PACKAGE LABEL

NDC 62106-1229-3

UNDA plex

ANGIPLEX
Homeopathic Preparation

For the temporary relief of sore throat and dry throat.

30 Tablets